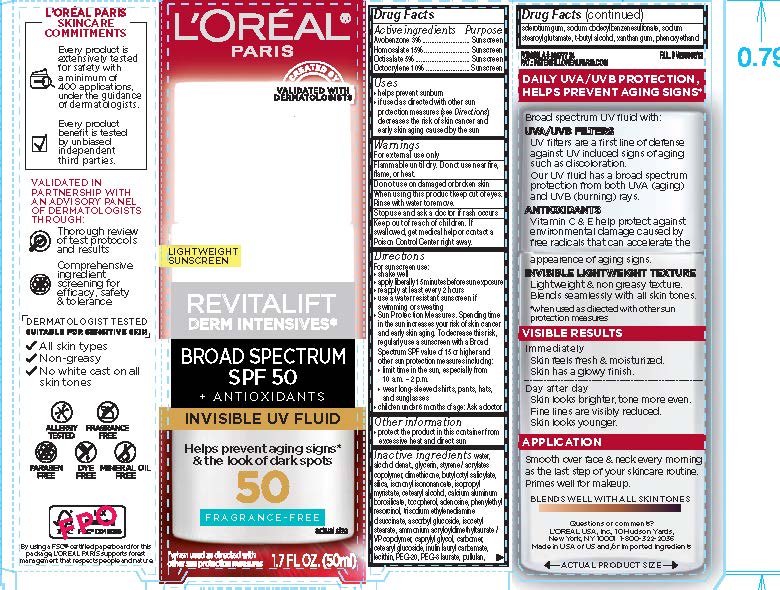 DRUG LABEL: LOreal Paris Revitalift Derm Intensives Invisible UV Fluid Broad Spectrum SPF 50 Sunscreen
NDC: 49967-011 | Form: GEL
Manufacturer: L'Oreal USA Products Inc
Category: otc | Type: HUMAN OTC DRUG LABEL
Date: 20241228

ACTIVE INGREDIENTS: Avobenzone 30 mg/1 mL; Homosalate 150 mg/1 mL; Octisalate 50 mg/1 mL; Octocrylene 100 mg/1 mL
INACTIVE INGREDIENTS: WATER; ALCOHOL; GLYCERIN; DIMETHICONE; BUTYLOCTYL SALICYLATE; SILICON DIOXIDE; ISONONYL ISONONANOATE; ISOPROPYL MYRISTATE; CETOSTEARYL ALCOHOL; CALCIUM ALUMINUM BOROSILICATE; TOCOPHEROL; TERT-BUTYL ALCOHOL; ASCORBYL GLUCOSIDE; HYDROGENATED SOYBEAN LECITHIN; SODIUM STEAROYL GLUTAMATE; SODIUM DODECYLBENZENESULFONATE; PHENOXYETHANOL; PHENYLETHYL RESORCINOL; ADENOSINE; PEG-8 LAURATE; POLYETHYLENE GLYCOL 1000; TRISODIUM ETHYLENEDIAMINE DISUCCINATE; BETASIZOFIRAN; PULLULAN; AMMONIUM ACRYLOYLDIMETHYLTAURATE/VP COPOLYMER; XANTHAN GUM; ISOCETYL STEARATE; CAPRYLYL GLYCOL; CARBOMER HOMOPOLYMER, UNSPECIFIED TYPE; CETEARYL GLUCOSIDE; INULIN LAURYL CARBAMATE

Drug Facts

Active ingredients

Avobenzone 3%

Homosalate 15%

Octisalate 5%

Octocrylene 10%

Purpose

Sunscreen

Uses

- helps prevent sunburn
- if used as directed with other sun protection measures (see Directions), decreases the risk of skin cancer and early skin aging caused by the sun

Warnings

For external use only

Flammable until dry.

Do not use near fire, flame, or heat.

Do not use

on damaged or broken skin

When using this product

keep out of eyes. Rinse with water to remove.

Stop use and ask a doctor if

rash occurs

Keep out of reach of children.

If swallowed, get medical help or contact a Poison Control Center right away.

Directions

For sunscreen use:

- shake well
- apply liberally 15 minutes before sun exposure
- reapply at least every 2 hours
- use a water resistant sunscreen if swimming or sweating
- Sun Protection Measures. Spending time in the sun increases your risk of skin cancer and early skin aging. To decrease this risk, regularly use a sunscreen with a Broad Spectrum SPF value of 15 or higher and other sun protection measures including:
- limit time in the sun, especially from 10 a.m. - 2 p.m.
- wear long-sleeved shirts, pants, hats, and sunglasses
- children under 6 months of age: Ask a doctor

Other information

protect the product in this container from excessive heat and direct sun

Inactive ingredients

water, alcohol denat., glycerin, styrene/acrylates copolymer dimethicone, butyloctyl salicylate, sodium dodecylbenzenesulfonate, phenoxyethanol, phenylethyl resorcinol, adenosine, PEG-8 laurate, PEG-20, trisodium ethylenediamine disuccinate, sclerotium gum, pullulan, ammonium acryloyldimethyltaurate/vp copolymer, xanthan gum, isocetyl stearate, caprylyl glycol, carbomer, cetearyl glucoside, inulin lauryl carbamate